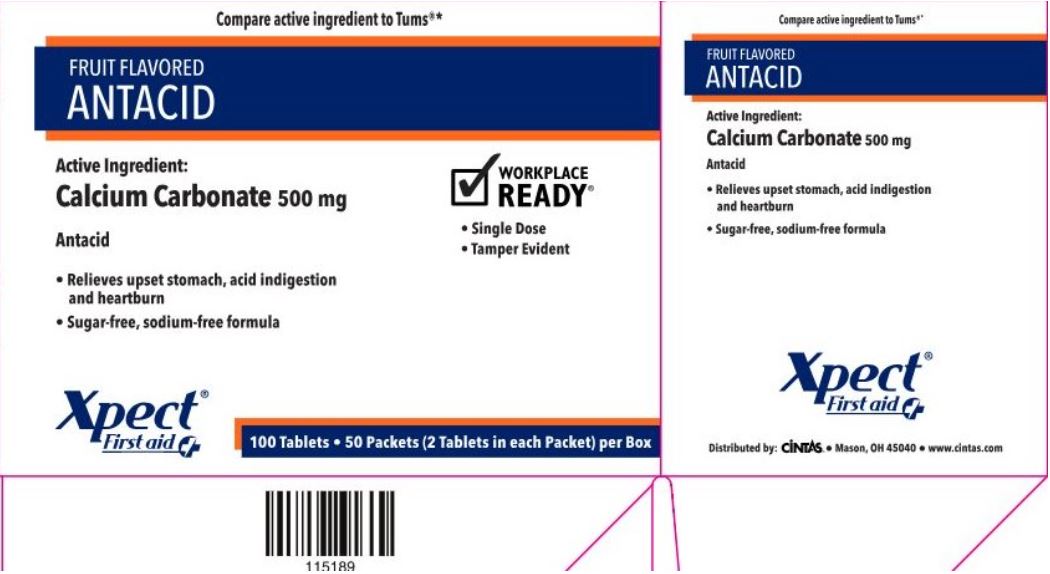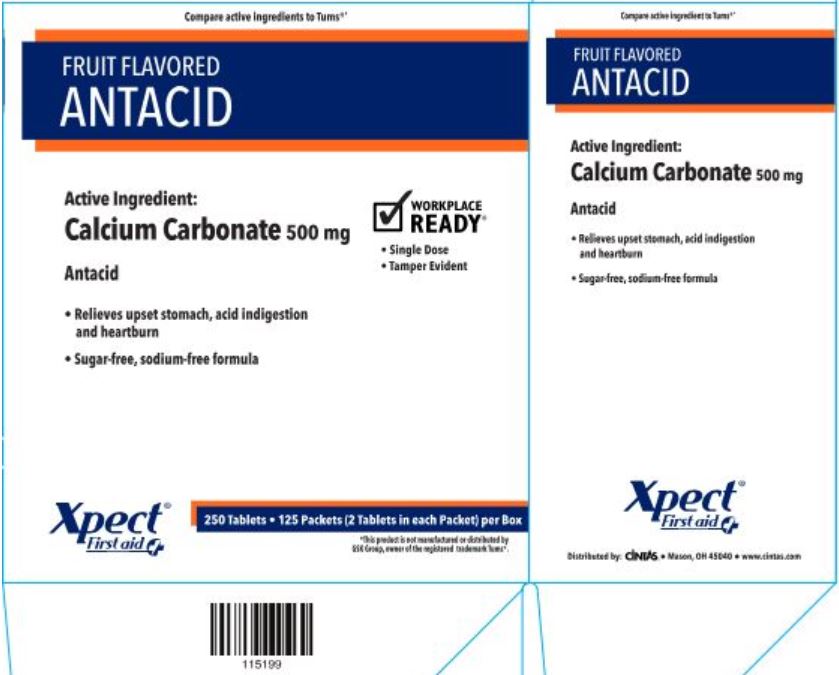 DRUG LABEL: Xpect Antacid
NDC: 42961-208 | Form: TABLET, CHEWABLE
Manufacturer: Cintas Corporation
Category: otc | Type: HUMAN OTC DRUG LABEL
Date: 20250922

ACTIVE INGREDIENTS: CALCIUM CARBONATE 500 mg/1 1
INACTIVE INGREDIENTS: FD&C YELLOW NO. 6; MAGNESIUM STEARATE; SORBITOL; MALTODEXTRIN

Xpect Antacid

Active ingredient (in each tablet)

Calcium carbonate USP 500mg

Purpose

Antacid

Uses

relieves

- heartburn
- sour stomach
- acid indigestion
- upset stomach associated with these symptoms

Warnings

Ask a doctor before use if you have

- kidney disease
- taking any prescription drugs; antacids may interact with certain precription drugs

When using this product do not take more than 15 tablets in a 24 hour period or use the maximum dosage of this product for more than 2 weeks.

Keep out of reach of children.

Directions

chew 2-4 tablets as symptoms occur, repeat hourly if needed

Other information

- store at 15°-30°C (59°-86°F)
- do not use if packet is open or torn
- Calcium content per tablets: 200 mg

Inactive ingredients

FD&C yellow #6 aluminum lake, magnesium stearate, maltodextrin, orange flavor, sorbitol

Principal Display Panel - 100 count Box

Compare active ingredient to Tums®*

FRUIT FLAVORED ANTACID

Active Ingredient:

Calcium Carbonate 500 mg

Antacid

- Relieves upset stomach, acid indigestion and heartburn
- Sugar-free, sodium-free formula

Xpect® First aid

WORKPLACE READY™

- Single Dose
- Tamper Evident

100 Tablets • 50 Packets (2 Tablets in each Packet) per Box

115189

Distributed by: CINTAS® • Mason, OH 45040 • www.cintas.com

Principal Display Panel - 250 count Box

Compare active ingredient to Tums®*
FRUIT FLAVORED ANTACID

Active Ingredient:

Calcium Carbonate 500 mg

Antacid

- Relieves upset stomach, acid indigestion and heartburn
- Sugar-free, sodium-free formula

Xpect® First aid

WORKPLACE READY™

- Single Dose
- Tamper Evident

250 Tablets • 125 Packets (2 Tablets in each Packet) per Box

115199

Distributed by: CINTAS® • Mason, OH 45040 • www.cintas.com